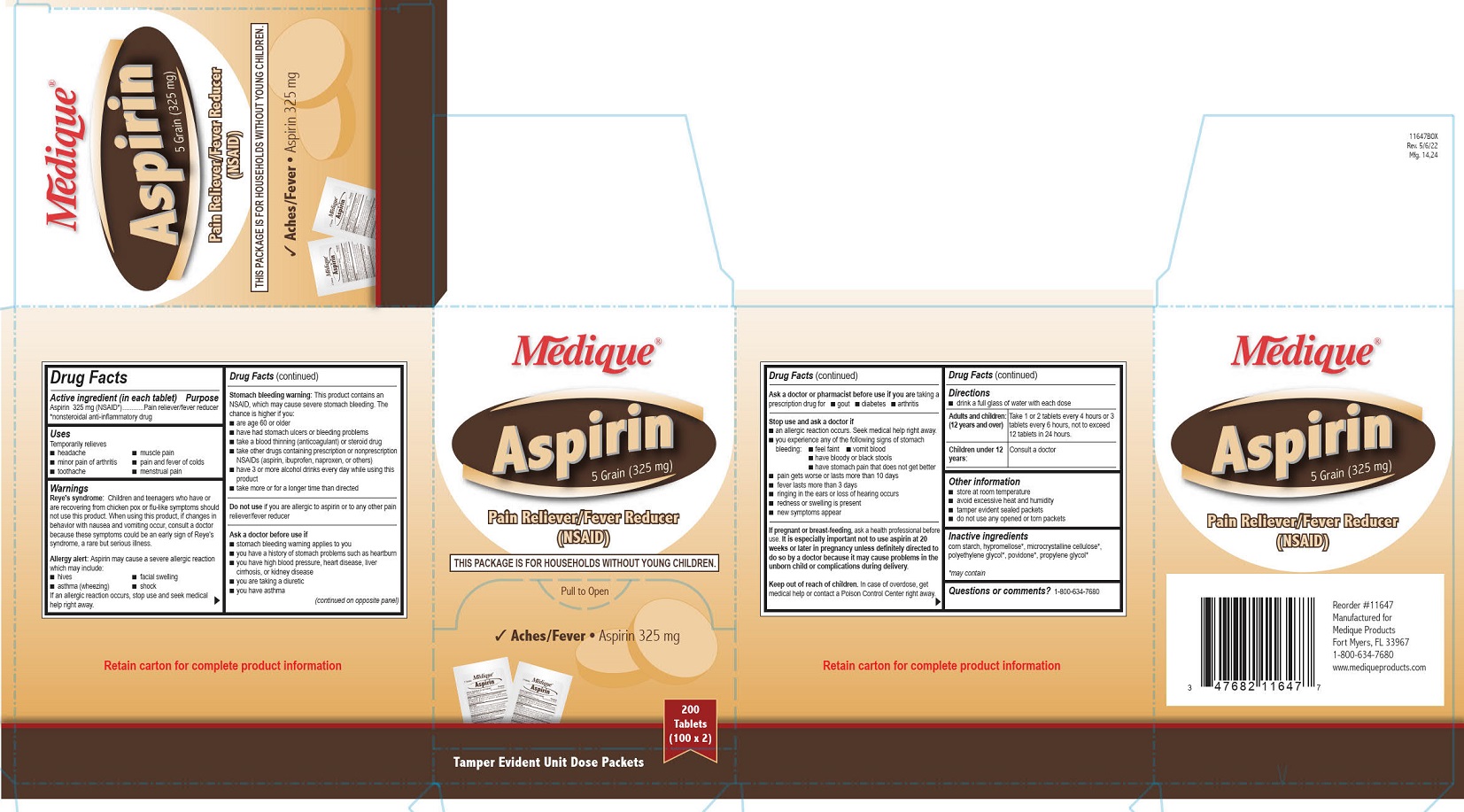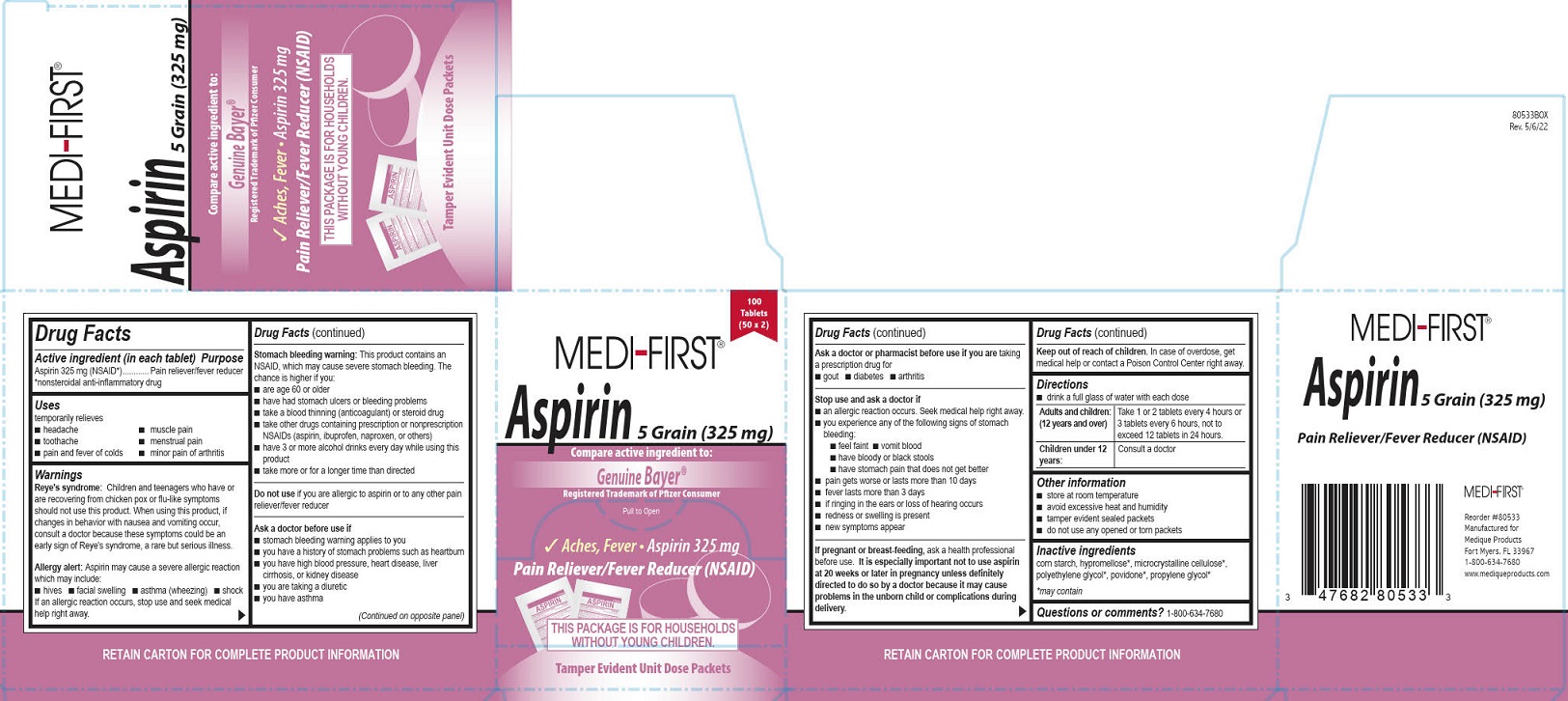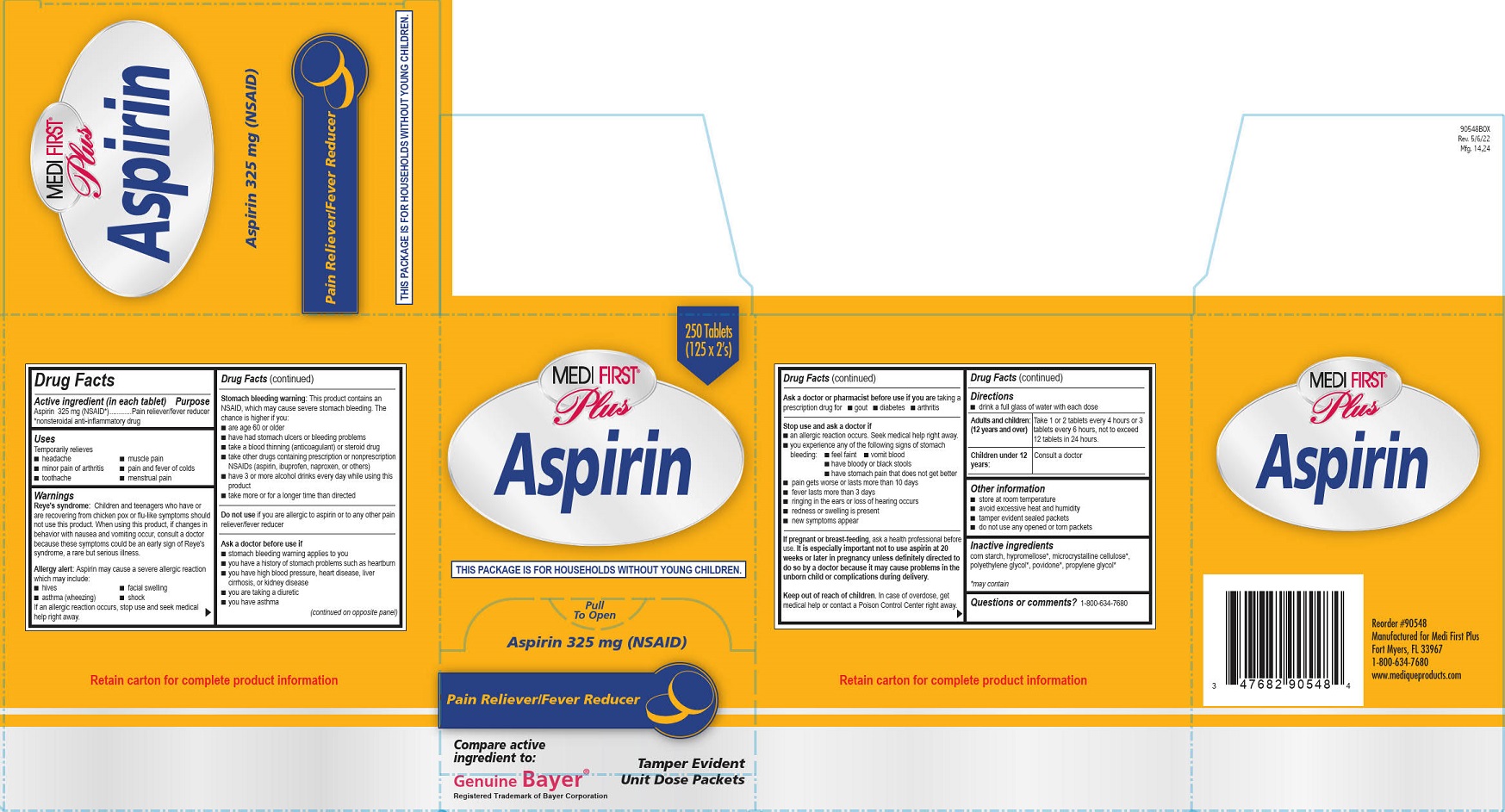 DRUG LABEL: Aspirin Packs
NDC: 70385-2006 | Form: TABLET, FILM COATED
Manufacturer: Sina Health Inc
Category: otc | Type: HUMAN OTC DRUG LABEL
Date: 20260112

ACTIVE INGREDIENTS: ASPIRIN 325 mg/1 1
INACTIVE INGREDIENTS: POLYETHYLENE GLYCOL, UNSPECIFIED; STARCH, CORN; HYPROMELLOSE, UNSPECIFIED; PROPYLENE GLYCOL

Medifirst Aspirin

Active ingredient (in each tablet)

Aspirin325 mg (NSAID*)

*nonsteroidal anti-inflammatory drug

Purpose

Pain reliever/fever reducer

Uses

Temporarily relieves

- headache
- toothache
- pain and fever of colds
- muscle pain
- menstrual pain
- minor pain of arthritis

Warnings

Reye's syndrome:Children and teenagers who have or are recovering from chicken pox or flu-like symptoms should not use this product. When using this product, if changes in behavior with nausea and vomiting occur, consult a doctor because these symptoms could be an early sign of Reye's syndrome, a rare but serious illness.

Allergy alert:Aspirin may cause a severe allergic reaction which may include:

- hives
- facial swelling
- asthma (wheezing)
- shock

If an allergic reaction occurs, stop use and seek medical help right away.

Stomach bleeding warning:

This product contains an NSAID, which may cause severe stomach bleeding. The chance is higher if you:

- are age 60 or older
- have had stomach ulcers or bleeding problems
- take a blood thinning (anticoagulant) or steroid drug
- take other drugs containing prescription or nonprescription NSAIDs (aspirin, ibuprofen, naproxen, or others)
- have 3 or more alcohol drinks every day while using this product
- take more or for a longer time than directed

DO NOT USE

Do not useif you are allergic to aspirin or to any other pain reliever/fever reducer

Ask a doctor before use if

- stomach bleeding warning applies to you
- you have a history of stomach problems such as heartburn
- you have high blood pressure, heart disease, liver cirrhosis, or kidney disease
- you are taking a diuretic
- you have asthma

Ask a doctor or pharmacist before use if you aretaking a prescription drug for

- gout
- diabetes
- arthritis

Stop use and ask a doctor if

- an allergic reaction occurs. Seek medical help right away.
- you experience any of the following signs of stomach bleeding:

■ feel faint ■ vomit blood ■ have bloody or black stools ■ have stomach pain that does not get better

- pain gets worse or lasts more than 10 days
- fever gets worse or lasts more than 3 days
- if ringing in the ears or loss of hearing occurs
- redness or swelling is present
- new symptoms appear

PREGNANCY OR BREAST FEEDING

If pregnant or breast-feeding,ask a health professional before use. It is especially important not to use aspirin at 20 weeks or later in pregnancy unless definately directed to do so by a doctor because it may cause problems in the unborn child or complications during delivery.

Keep out of reach of children.In case of overdose, get medical help or contact a Poison Control Center right away.

Directions

- drink a full glass of water with each dose

Adults and children:Take 1 or 2 tablets every 4 hours or 3 tablets every 6 hours, not to exceed 12 tablets in 24 hours.
(12 years and over)

Children under 12 years:Consult a doctor

Other information

- store at room temperature
- avoid excessive heat and humidity
- tamper evident sealed packets
- do not use any opened or torn packets

Inactive ingredients

corn starch, hypromellose*, microcrystalline cellulose*, polyethylene glycol*, povidone*, propylene glycol*

*m ay contain

Questions or comments?1-800-634-76870

Medique Products Aspirin Label

Medique®

Aspirin

5 Grain (325 mg)

Pain Reliever/Fever Reducer

(NSAID)

This Package is for Households without Young Children.

Pull to Open

Aches/Fever • Aspirin 325 mg

200 Tablets (100 x 2)

Tamper Evident Unit Dose Packets

Medi-First Aspirin Label

100 Tablets

(50 x 2)

Medi-First®

Aspirin 5 Grain (325 mg)

Compare Acrive Ingredients to:

Genuine Bayer®

Registered Trademark of Pfizer Consumer

Pull To Open

Aches, Fever • Aspirin 325 mg

Pain Reliever/Fever Reducer (NSAID)

This Package is for Households without Young Children.

Tamper Evident Unit Dose Packets

Medi-First Plus Aspirin Label

250 Tablets

(125 x 2's)

Medi First® Plus

Aspirin

This Package is for Households without Young Children.

Pull To Open

Aspirin 325 mg (NSAID)

Pain Reliever/Fever Reducer

Compare active ingredient to:

Genuine Bayer®

Registered Trademark of Bayer Corporation

Tamper Evident Unit Dose Packets

PACKAGE LABEL

Medique®

Aspirin

5 Grain (325 mg)

Pain Reliever/Fever Reducer

(NSAID)

This Package is for Households without Young Children.

Pull to Open

Aches/Fever • Aspirin 325 mg

200 Tablets (100 x 2)

Tamper Evident Unit Dose Packets

PACKAGE LABEL

100 Tablets

(50 x 2)

Medi-First®

Aspirin 5 Grain (325 mg)

Compare Active Ingredients to:

Genuine Bayer®

Registered Trademark of Pfizer Consumer

Pull To Open

Aches, Fever • Aspirin 325 mg

Pain Reliever/Fever Reducer (NSAID)

This Package is for Households without Young Children.

Tamper Evident Unit Dose Packets

PACKAGE LABEL

250 Tablets

(125 x 2's)

Medi First® Plus

Aspirin

This Package is for Households without Young Children.

Pull To Open

Aspirin 325 mg (NSAID)

Pain Reliever/Fever Reducer

Compare active ingredient to:

Genuine Bayer®

Registered Trademark of Bayer Corporation

Tamper Evident Unit Dose Packets